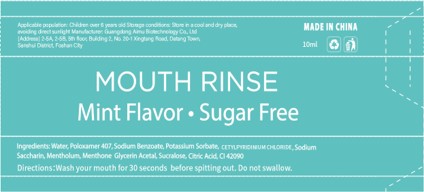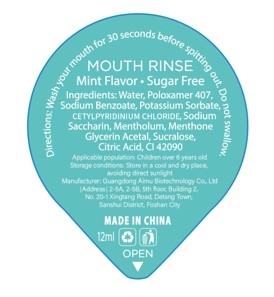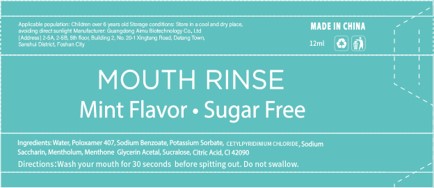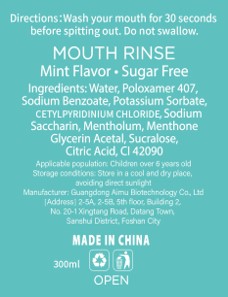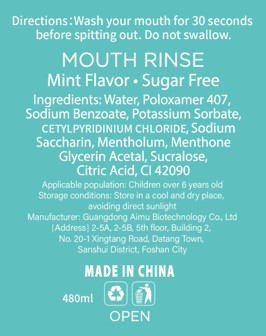 DRUG LABEL: Mouth Rinse
NDC: 83566-201 | Form: LIQUID
Manufacturer: Guangdong Aimu Biological Technology Co., Ltd
Category: otc | Type: HUMAN OTC DRUG LABEL
Date: 20231120

ACTIVE INGREDIENTS: MENTHOL 0.02 g/100 mL; MENTHONE 1,2-GLYCEROL KETAL, (+/-)- 0.005 g/100 mL
INACTIVE INGREDIENTS: ANHYDROUS CITRIC ACID; WATER; CETYLPYRIDINIUM CHLORIDE; POLOXAMER 407; POTASSIUM SORBATE; SUCRALOSE; SODIUM BENZOATE; SACCHARIN; DISODIUM N-ETHYL-N-4-((4-(ETHYL((3-SULFOPHENYL)METHYL)AMINO)PHENYL)(2-SULFOPHENYL)METHYLENE)-2,5-CYCLOHEXADIEN-1-YLIDENE)-3-SULFOBENZENEMETHANAMINIUM

MOUTH RINSE

MOUTH RINSE

ACTIVE INGREDIENT

MENTHOLUM 0.02% MENTHONE GLYCERIN ACETAL 0.005%

PURPOSE

Clean the oral cavity and prevent oral diseases

INDICATIONS AND USAGE

Directions:Wash your mouth for 30 secondsbefore spitting out. Do not swallow.

WARNINGS

Do not swallow, please keep out of reach of children.
For use only by people aged six and above.

Do not use under the age of six, and do not use if there is a wound in the mouth.

WHEN USING

Directions:Wash your mouth for 30 secondsbefore spitting out. Do not swallow.

STOP USE

If adverse reactions occur during use, please seek medical assistance immediately.

Keep out of reach of children.

DOSAGE AND ADMINISTRATION

Applicable population: Children over 6 years oldStorage conditions: Store in a cool and dry place,avoiding direct sunlight

STORAGE AND HANDLING

Storage conditions: Store in a cool and dry place,avoiding direct sunlight

INACTIVE INGREDIENT

WATER
CETYLPYRIDINIUM CHLORIDE
POLOXAMER 407
POTASSIUM SORBATE
SUCRALOSE
SODIUM BENZOATE
SODIUM SACCHARIN
CITRIC ACID
CI42090